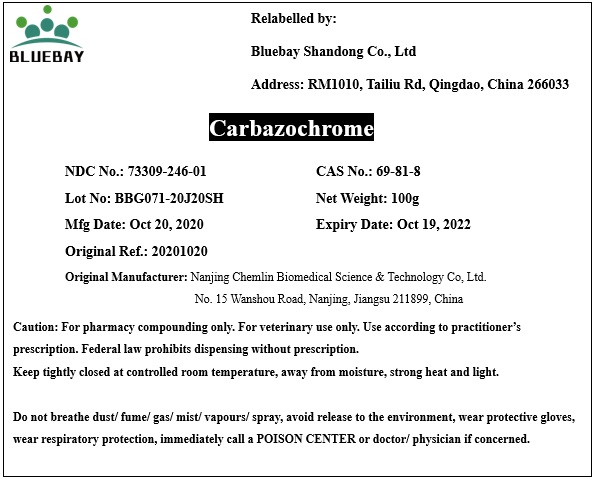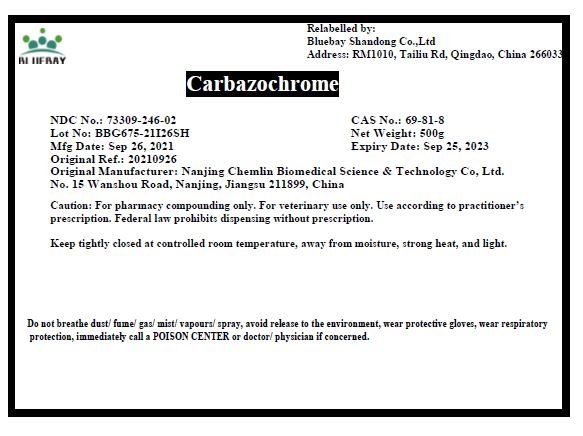 DRUG LABEL: Carbazochrome
NDC: 73309-246 | Form: POWDER
Manufacturer: BLUEBAY SHANDONG CO.,LTD
Category: other | Type: BULK INGREDIENT
Date: 20211222

ACTIVE INGREDIENTS: CARBAZOCHROME 1 g/1 g

Carbazochrome